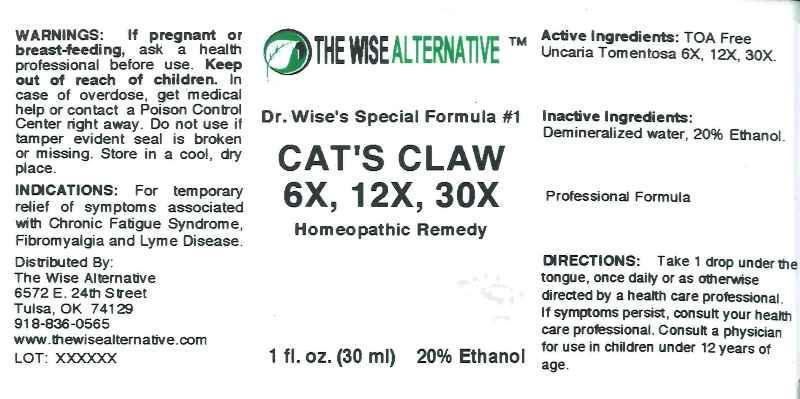 DRUG LABEL: Dr. Wise Special Formula
NDC: 51096-0005 | Form: LIQUID
Manufacturer: J and L Health LLC dba The Wise Alternative
Category: homeopathic | Type: HUMAN PRESCRIPTION DRUG LABEL
Date: 20120927

ACTIVE INGREDIENTS: CAT'S CLAW 6 [hp_X]/1 mL
INACTIVE INGREDIENTS: WATER; ALCOHOL

DRUG FACTS

ACTIVE INGREDIENTS

Toa Free Uncaria Tomentosa 6X, 12X, 30X.

INDICATIONS

For temporary relief of symptoms associated with Chronic Fatigue Syndrome, Fibromyalgia and Lyme Disease.

WARNINGS SECTION

If pregnant or breast-feeding, ask a health professional before use. Keep out of reach of children. In case of overdose, get medical help or contact a Poison Control Center right away. Do not use if tamper evident seal is broken or missing. Store in cool, dry place.

DIRECTIONS

Take 1 drop under the tongue, once daily or as otherwise directed by a health care professional. If symptoms persist, consult your health care profesional. Consult a physician for use in children under 12 years of age.

INACTIVE INGREDIENTS

Demineralized water, 20% Ethanol.

KEEP OUT OF REACH OF CHILDREN

In case of overdose, get medical help or contact a Poison Control Center right away.

INDICATIONS AND USAGE

For temporary relief of symptoms associated with Chronic Fatigue Syndrome, Fibromyalgia and Lyme Disease.

QUESTIONS

Distributed By:

The Wise Alternative

6572 E. 24th Street

Tulsa, OK 74129

918-836-0565

www.thewisealternative.com

PACKAGE LABEL

THE WISE ALTERNATIVE

Dr. Wise Special Formula 1

CAT'S CLAW 6X, 12X, 30X

Homeopathic Remedy

1 fl oz (30 ml)